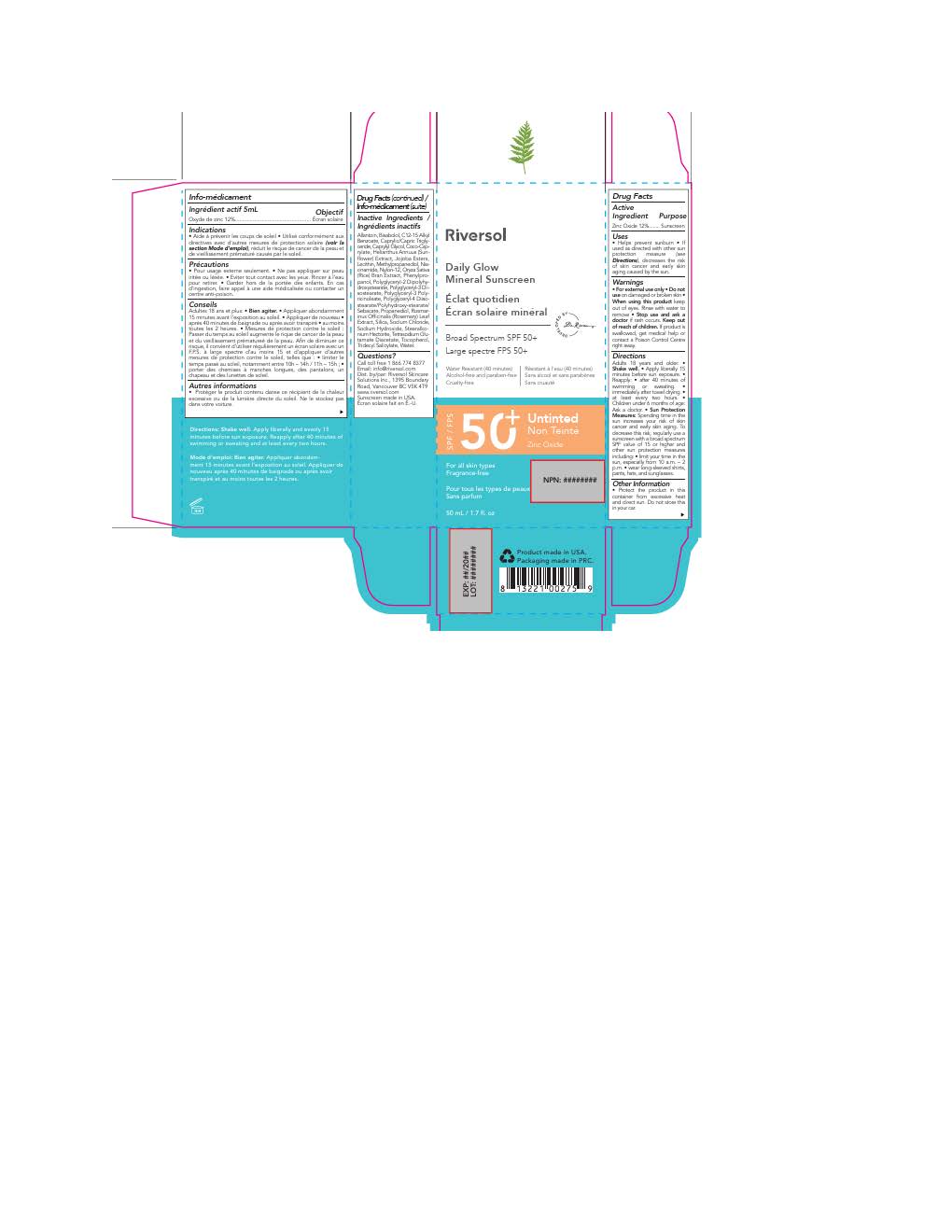 DRUG LABEL: Riversol Daily Glow Mineral Untinted
NDC: 72019-2033 | Form: LOTION
Manufacturer: Riversol Skincare
Category: otc | Type: HUMAN OTC DRUG LABEL
Date: 20251117

ACTIVE INGREDIENTS: ZINC OXIDE 132 mg/1 mL
INACTIVE INGREDIENTS: ORYZA SATIVA WHOLE; TRIDECYL SALICYLATE; SILICON DIOXIDE; TOCOPHEROL; CAPRYLYL GLYCOL; COCO-CAPRYLATE; NYLON-12; PHENYLPROPANOL; HELIANTHUS ANNUUS FLOWERING TOP; LECITHIN, SOYBEAN; METHYLPROPANEDIOL; POLYGLYCERYL-2 DIPOLYHYDROXYSTEARATE; JOJOBA OIL; ALLANTOIN; ALKYL (C12-15) BENZOATE; ROSMARINUS OFFICINALIS FLOWER; .ALPHA.-BISABOLOL, (+)-; SODIUM HYDROXIDE; WATER; NIACINAMIDE; PROPANEDIOL; TETRASODIUM GLUTAMATE DIACETATE; SODIUM CHLORIDE; POLYGLYCERYL-4 DIISOSTEARATE/POLYHYDROXYSTEARATE/SEBACATE; POLYGLYCERYL-3 DIISOSTEARATE; STEARALKONIUM HECTORITE

Riversol Daily Glow Mineral Untinted